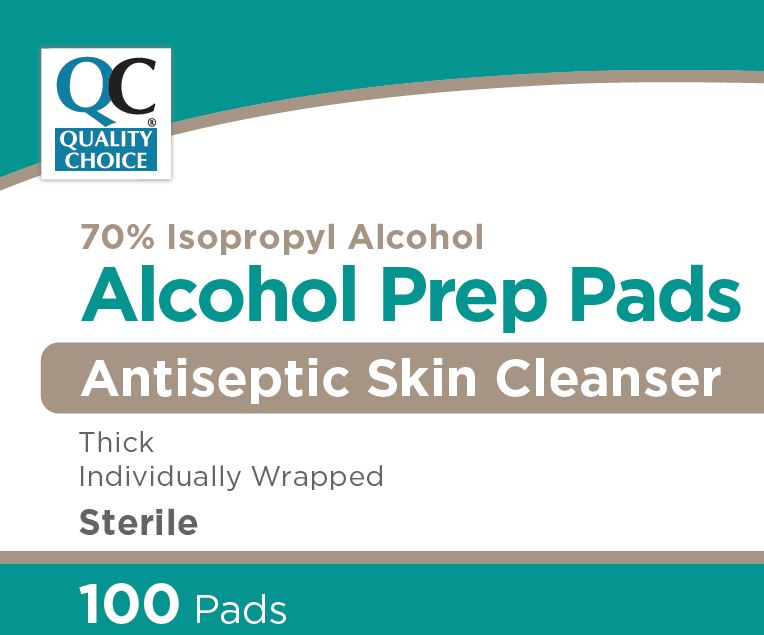 DRUG LABEL: Sterile Alcohol
NDC: 63868-980 | Form: SWAB
Manufacturer: Chain Drug Marketing Association Inc
Category: otc | Type: HUMAN OTC DRUG LABEL
Date: 20250103

ACTIVE INGREDIENTS: ISOPROPYL ALCOHOL 0.7 mL/1 1
INACTIVE INGREDIENTS: WATER

63868-980 Chain Drug Marketing Association IPA Pad

Active ingredient

Isopropyl alcohol 70% v/v

Purpose

Antiseptic

Uses

- • first aid to decrease germs in minor cuts, scrapes and burns

Warnings

For external use only.

Flammable. Keep away from fire or flame.

Do not use

- • with electrocautery procedures
- • longer than 1 week unless directed by a doctor

When using this product

- • do not get into eyes
- • do not apply over large areas of the body
- • in case of deep or puncture wounds, animal bites or serious burns, consult a doctor

Stop use and ask a doctor if

- • irritation and redness develop
- • condition gets worse or persists for more than 72 hours

Keep our of reach of children.

If accidentally swallowed, get medical help or contact a Poison Control Center right away.

Directions

- • apply topically as needed
- • discard after a single use

Other information

- • protect from freezing and avoid excessive heat
- • not made with natural rubber latex

Inactive ingredients

water

Manufacturing Information

Distributed by:

C.D.M.A., Inc.

43157 W 9 Mile Road, Novi, MI 48375

Made in China

248-449-9300

www.qualitychoice.com

REF: CDMA1001

V1 RD20LPD